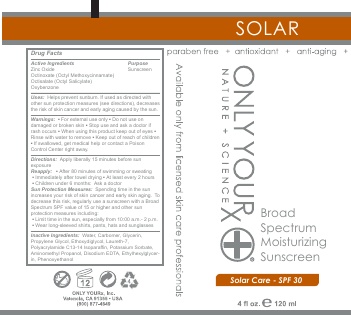 DRUG LABEL: Broad Spectrum Moisturizing Sunscreen SPF 30
NDC: 70367-005 | Form: LOTION
Manufacturer: Only Yourx, Inc.
Category: otc | Type: HUMAN OTC DRUG LABEL
Date: 20200123

ACTIVE INGREDIENTS: OCTINOXATE 6.75 g/100 mL; ZINC OXIDE 7.2 g/100 mL; OCTISALATE 2.7 g/100 mL; OXYBENZONE 4.5 g/100 mL
INACTIVE INGREDIENTS: DIISOPROPYL SEBACATE; GREEN TEA LEAF; LICORICE; XANTHAN GUM; MAGNESIUM ALUMINUM SILICATE; PHENOXYETHANOL; ETHYLHEXYLGLYCERIN; ISODECYL NEOPENTANOATE; LAURYL LACTATE; GLYCERIN; STEARYL ALCOHOL; CETYL ALCOHOL; SQUALANE; POLYSORBATE 60; SODIUM ACRYLOYLDIMETHYLTAURATE

Active Ingredients: Octinoxate, Zinc Oxide, Octisalate, Oxybenzone

INACTIVE INGREDIENT

Other Ingredients: Water, Isodecyl Neopentanoate, Diisopropyl Sebacate, Lauryl Lactate, Glycerin, Stearyl Alcohol, Cetyl Alcohol, Squalane, Polysorbate 60, Vitamin E Tocopheryl Acetate, Pine Bark Extract, Japanese Green Tea Extract, Rosehips Extract, Licorice Extract, Sodium Edetate, Xanthan Gum, Magnesium Aluminum Silicate, Phenoxyethanol, Ethylhexyiglycerin, Hydroethylacrylate/Sodium Acryloldimethyl Copolymer, Fragrance

OTHER SAFETY INFORMATION

Suitable for normal to dry skin

DOSAGE AND ADMINISTRATION

Apply a liberal amount approximately 30 minutes prior to sun exposure. For continuous protection, reapply regularly and after swimming and/or exercising.

INDICATIONS AND USAGE

Vitamin-enriched formula skin-aging UVA/UVB rays with advanced, broad-spectrum sunscreens and powerful antioxidants. Helps prevent moisture loss and premature aging of the skin.

PURPOSE

Broad spectrum UVA and UVB protection.

WARNINGS

Warnings: For external use only; Do not use on damaged or broken skin; Stop use and ask a doctor if rash occurs; When using this product keep out of eyes; Rinse with water to remove;

Keep out of reach of children; If swallowed, get medical help or contact a Poison Control Center immediately